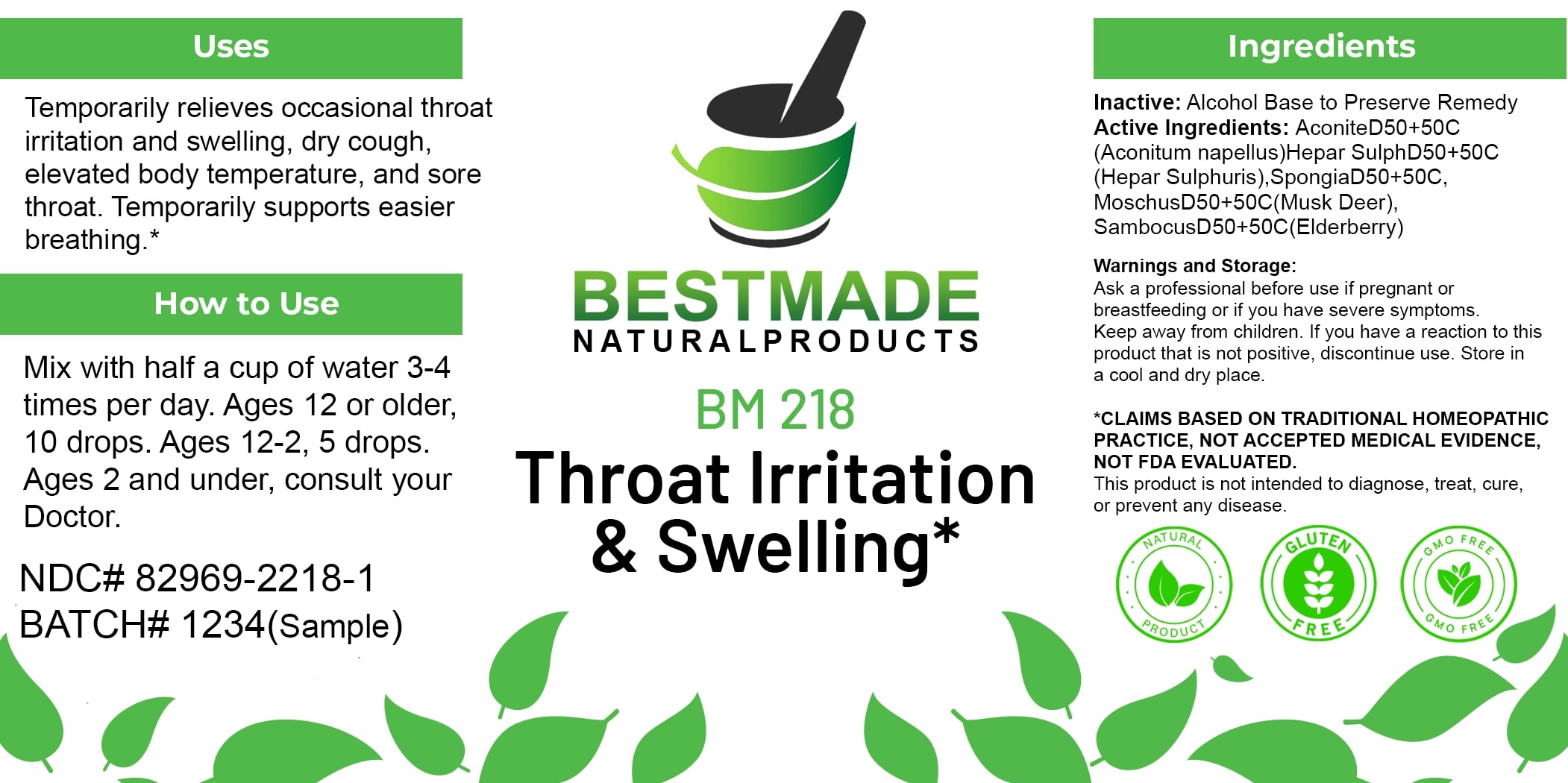 DRUG LABEL: Bestmade Natural Products BM218
NDC: 82969-2218 | Form: LIQUID
Manufacturer: Bestmade Natural Products
Category: homeopathic | Type: HUMAN OTC DRUG LABEL
Date: 20250303

ACTIVE INGREDIENTS: SAMBUCUS NIGRA FLOWERING TOP 50 [hp_C]/50 [hp_C]; SPONGIA OFFICINALIS SKELETON, ROASTED 50 [hp_C]/50 [hp_C]; MOSCHUS MOSCHIFERUS MUSK SAC RESIN 50 [hp_C]/50 [hp_C]; ACONITUM NAPELLUS 50 [hp_C]/50 [hp_C]; CALCIUM SULFIDE 50 [hp_C]/50 [hp_C]
INACTIVE INGREDIENTS: ALCOHOL 50 [hp_C]/50 [hp_C]

BM218

DOSAGE AND ADMINISTRATION

How to Use

Mix with half a cup of water 3-4 times per day. Ages 12 or older, 10 drops. Ages 12-2, 5 drops. Ages 2 and under, consult your Doctor.

Uses

Temporarily relieves occasional throat irritation and swelling, dry cough, elevated body temperature, and sore throat. Temporarily supports easier breathing.*

*CLAIMS BASED ON TRADITIONAL HOMEOPATHIC PRACTICE, NOT ACCEPTED MEDICAL EVIDENCE. NOT FDA EVALUATED.

This product is not intended to diagnose, treat, cure, or prevent any disease.

INACTIVE INGREDIENT

Ingredients

Inactive: Alcohol Base to Preserve Remedy

ACTIVE INGREDIENT

Active Ingredients: AconiteD50+50C (Aconitum napellus), Hepar SulphD50+50C (Hepar Sulphuris), SpongiaD50+50C, MoschusD50+50C(Musk Deer), SambucusD50+50C(Elderberry)

KEEP OUT OF REACH OF CHILDREN

Warnings and Storage:

Ask a professional before use if pregnant or breastfeeding or if you have severe symptoms. Keep away from children. If you have a reaction to this product that is not positive, discontinue use. Store in a cool and dry place.

Warnings and Storage:

Ask a professional before use if pregnant or breastfeeding or if you have severe symptoms. Keep away from children. If you have a reaction to this product that is not positive, discontinue use. Store in a cool and dry place.

*CLAIMS BASED ON TRADITIONAL HOMEOPATHIC PRACTICE, NOT ACCEPTED MEDICAL EVIDENCE. NOT FDA EVALUATED.

This product is not intended to diagnose, treat, cure, or prevent any disease.

Uses

Temporarily relieves occasional throat irritation and swelling, dry cough, elevated body temperature, and sore throat. Temporarily supports easier breathing.*

*CLAIMS BASED ON TRADITIONAL HOMEOPATHIC PRACTICE, NOT ACCEPTED MEDICAL EVIDENCE. NOT FDA EVALUATED.

This product is not intended to diagnose, treat, cure, or prevent any disease.

Entire package label